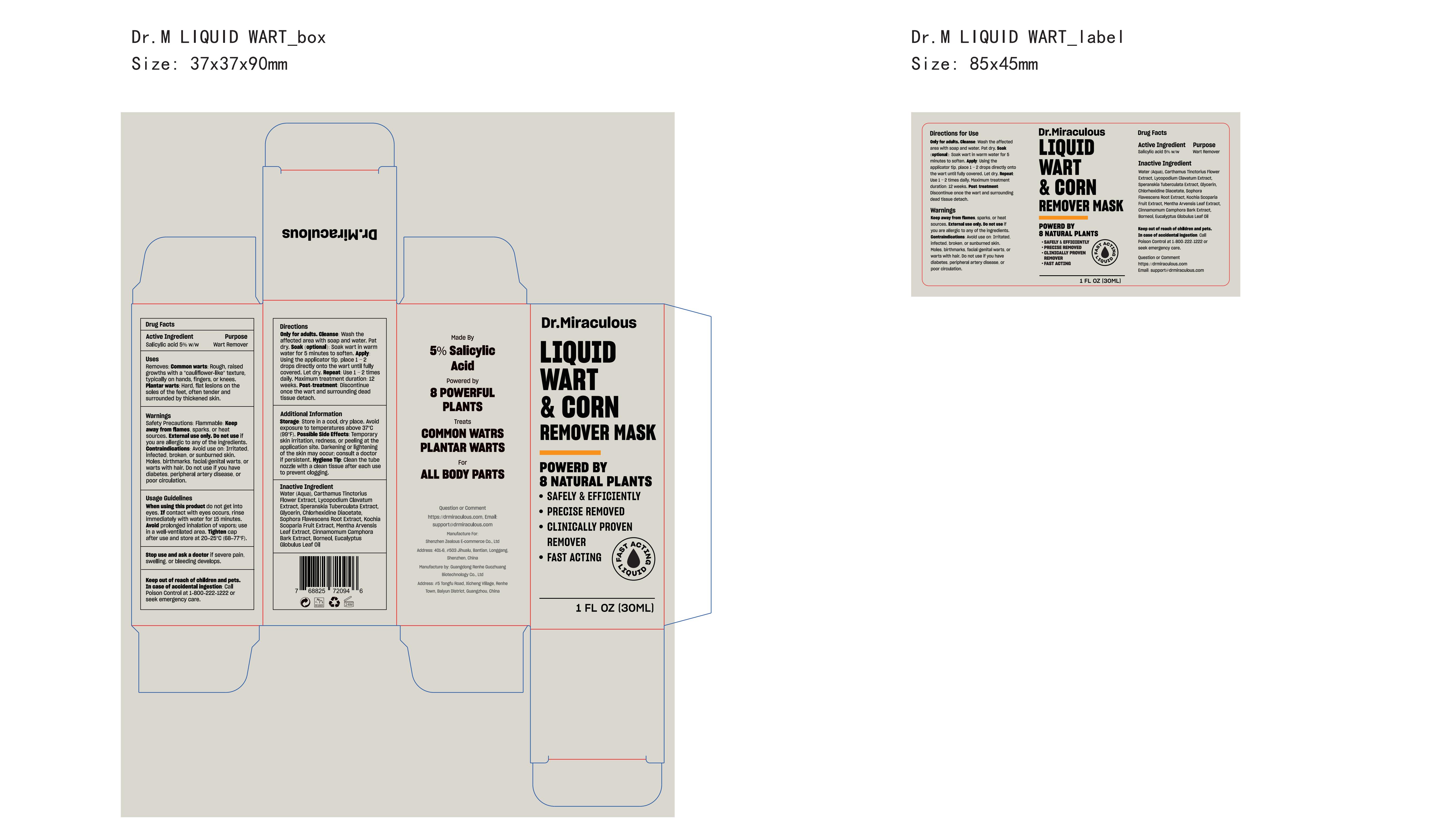 DRUG LABEL: Dr.Miraculous Wart Remover Liquid
NDC: 85587-003 | Form: LIQUID
Manufacturer: Shenzhen Zealous Ecommerce Technology Co., Ltd
Category: otc | Type: HUMAN OTC DRUG LABEL
Date: 20250509

ACTIVE INGREDIENTS: SALICYLIC ACID 5 g/100 mL
INACTIVE INGREDIENTS: BORNEOL; SPERANSKIA TUBERCULATA WHOLE; MENTHA ARVENSIS LEAF; CARTHAMUS TINCTORIUS (SAFFLOWER) FLOWER; LYCOPODIUM CLAVATUM SPORE; GLYCERIN; CHLORHEXIDINE DIACETATE; BASSIA SCOPARIA FRUIT; EUCALYPTUS GLOBULUS LEAF OIL; CINNAMOMUM CASSIA BARK; WATER; SOPHORA FLAVESCENS ROOT

85587-003

Active Ingredient

Salicylic acid 5% w/w

Purpose

Wart Remover

Use

Removes: Common warts: Rough, raised growths with a "cauliflower-like" texture, typically on hands, fingers, or knees. Plantar warts: Hard, flat lesions on the soles of the feet, often tender and surrounded by thickened skin.

Warnings

Safety Precautions: Flammable. Keep away from flames, sparks, or heat sources. External use only. Do not apply to eyes, mouth, or mucous membranes.

Do not use

Avoid use on: Irritated, infected, broken, or sunburned skin. Moles, birthmarks, facial/genital warts, or warts with hair. Do not use if you have diabetes, peripheral artery disease, or poor circulation.

When Using

Wash the affected area with soap and water. Pat dry. Soak wart in warm water for 5 minutes to soften.

Stop Use

Discontinue once the wart and surrounding dead tissue detach or after the maximum treatment duration of 12 weeks.

Ask Doctor

Consult a doctor if persistent, as possible side effects include temporary skin irritation, redness, or peeling at the application site. Darkening or lightening of the skin may also occur.

Keep Out Of Reach Of Children

Directions

Using the applicator tip, place 1–2 drops directly onto the wart until fully covered. Let dry. Use 1–2 times daily.

Inactive ingredients

Water (Aqua), Carthamus Tinctorius Flower Extract, Lycopodium Clavatum Extract, Speranskia Tuberculata Extract, Glycerin, Chlorhexidine Diacetate, Sophora Flavescens Root Extract, Kochia Scoparia Fruit Extract, Mentha Arvensis Leaf Extract, Cinnamomum Camphora Bark Extract, Borneol, Eucalyptus Globulus Leaf Oil

Questions

Website: https://drmiraculous.com Email: support@drmiraculous.com